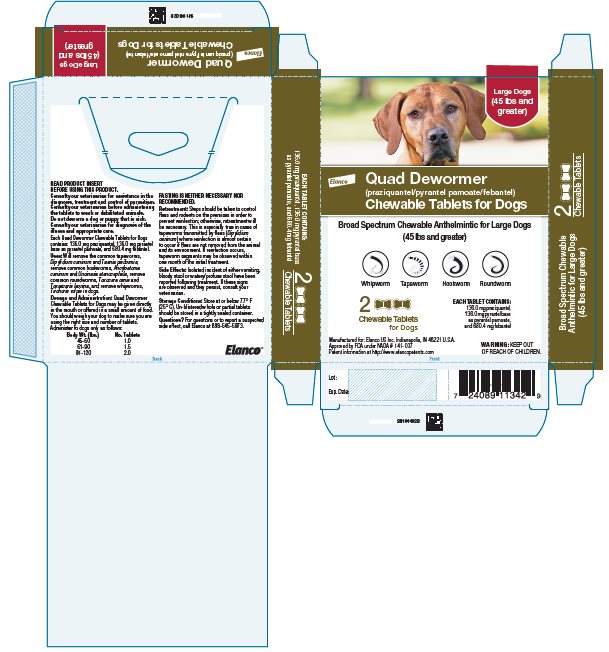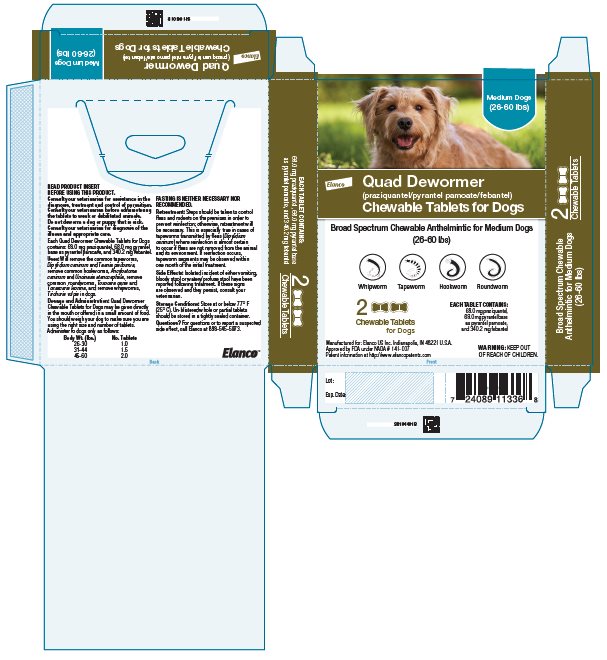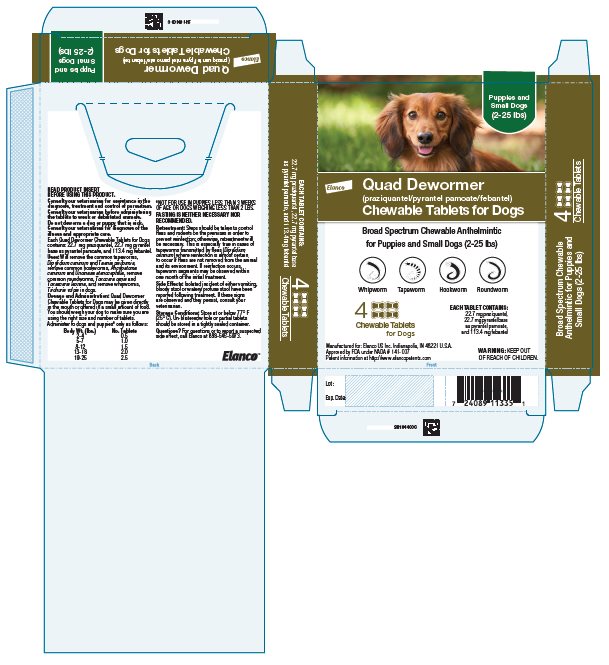 DRUG LABEL: Quad Dewormer
NDC: 58198-0056 | Form: TABLET, CHEWABLE
Manufacturer: Elanco US Inc.
Category: animal | Type: OTC ANIMAL DRUG LABEL
Date: 20260224

ACTIVE INGREDIENTS: PRAZIQUANTEL 22.7 mg/1 1; PYRANTEL PAMOATE 22.7 mg/1 1; FEBANTEL 113.4 mg/1 1

Elanco™
Quad Dewormer
(praziquantel/pyrantel pamoate/febantel)

Chewable Tablets for Dogs

PA104400X

Consult your veterinarian for assistance in the diagnosis, treatment and control of parasitism. Consult your veterinarian before administering the tablets to weak or debilitated animals. Do not deworm a dog or puppy that is sick. Consult your veterinarian for diagnosis of the illness and appropriate care.

Each Quad Dewormer Chewable Tablets for Puppies and Small Dogs contains 22.7 mg praziquantel, 22.7 mg pyrantel base as pyrantel pamoate and 113.4 mg febantel.

Each Quad Dewormer Chewable Tablets for Medium Dogs contains 68.0 mg praziquantel, 68.0 mg pyrantel base as pyrantel pamoate and 340.2 mg febantel.

Each Quad Dewormer Chewable Tablets for Large Dogs contains 136.0 mg praziquantel, 136.0 mg pyrantel base as pyrantel pamoate, and 680.4 mg febantel.

DESCRIPTION:

Quad Dewormer (praziquantel/pyrantel pamoate/febantel) Chewable Tablets for Dogs are available in three tablet sizes. Each size is scored for convenient oral administration.

USES:

Quad Dewormer (praziquantel/pyrantel pamoate/febantel) Chewable Tablets for Dogs will remove the common tapeworms, Dipylidium caninum and Taenia pisiformis, remove common hookworms, Ancylostoma caninum and Uncinaria stenocephala, remove common roundworms, Toxocara canis and Toxascaris leonina, and remove whipworms, Trichuris vulpis in dogs.

WARNING:

KEEP OUT OF REACH OF CHILDREN.

USE DIRECTIONS

DOSAGE AND ADMINISTRATION:

Quad Dewormer Chewable Tablets for Dogs may be given directly in the mouth or offered in a small amount of food. You should weigh your dog to make sure you are using the right size and number of tablets. Administer to dogs and puppies* only as follows:

Quad Dewormer Chewable Tablets for Dogs Dosage Charts
for Puppies and Small Dogs*
(2 - 25 lbs.)
Body Wt. (lbs.) | No. of Tablets
2 - 4 | 0.5
5 - 7 | 1.0
8 - 12 | 1.5
13 - 18 | 2.0
19 - 25 | 2.5
for Medium Dogs
(26 - 60 lbs.)
Body Wt. (lbs.) | No. of Tablets
26 - 30 | 1.0
31 - 44 | 1.5
45 - 60 | 2.0
for Large Dogs
(45 lbs. and greater)
Body Wt. (lbs.) | No. of Tablets
45 - 60 | 1.0
61 - 90 | 1.5
91 - 120 | 2.0
*NOT FOR USE IN PUPPIES LESS THAN 3 WEEKS OF AGE OR DOGS WEIGHING LESS THAN 2 LBS.

FASTING IS NEITHER NECESSARY NOR RECOMMENDED.

RETREATMENT:

Steps should be taken to control fleas and rodents on the premises in order to prevent reinfection; otherwise, retreatment will be necessary. This is especially true in cases of tapeworms transmitted by fleas (Dipylidium caninum) where reinfection is almost certain to occur if fleas are not removed from the animal and its environment. If reinfection occurs, tapeworm segments may be observed within one month of the initial treatment.

SIDE EFFECTS:

Isolated incident of either vomiting, bloody stool or watery/profuse stool have been reported following treatment. If these signs are observed and they persist, consult your veterinarian.

Questions?

For questions or to report a suspected side effect, call Elanco at 888-545-5973.

STORAGE CONDITIONS:

Store at or below 77 °F (25 °C).

Un-blistered whole or partial tablets should be stored in a tightly sealed container.

HOW SUPPLIED:

Quad Dewormer Chewable Tablets for Dogs are available in three tablet sizes:

4 tabs/box for Puppies and Small Dogs

2 tabs/box for Medium Dogs

2 tabs /box for Large Dogs

Manufactured for:
Elanco US Inc.
Indianapolis, IN 46221 U.S.A.

Elanco and the diagonal bar logo are trademarks of Elanco or its affiliates.

© 2025 Elanco or its affiliates

Approved by FDA under NADA # 141-007

Patent information at http://www.elancopatents.com

August 2025

Elanco™

Principal Display Panel – Large Dogs Carton Label

Elanco

Quad Dewormer

(praziquantel/pyrantel pamoate/febantel)

Chewable Tablets for Dogs

Broad Spectrum Chewable Anthelmintic for Large Dogs
(45 lbs and greater)

Whipworm
Tapeworm
Hookworm
Roundworm

2
Chewable Tablets
for Dogs

EACH TABLET CONTAINS:

136.0 mg praziquantel,
136.0 mg pyrantel base
as pyrantel pamoate,
and 680.4 mg febantel

Manufactured for: Elanco US Inc. Indianapolis, IN 46221 U.S.A.
Approved by FDA under NADA # 141-007
Patent information at http://www.elancopatents.com

WARNING: KEEP OUT
OF REACH OF CHILDREN.

Principal Display Panel – Medium Dogs Carton Label

Elanco

Quad Dewormer

(praziquantel/pyrantel pamoate/febantel)

Chewable Tablets for Dogs

Broad Spectrum Chewable Anthelmintic for Medium Dogs
(26-60 lbs)

Whipworm
Tapeworm
Hookworm
Roundworm

2
Chewable Tablets
for Dogs

EACH TABLET CONTAINS:

68.0 mg praziquantel,
68.0 mg pyrantel base
as pyrantel pamoate,
and 340.2 mg febantel

Manufactured for: Elanco US Inc. Indianapolis, IN 46221 U.S.A.
Approved by FDA under NADA # 141-007
Patent information at http://www.elancopatents.com

WARNING: KEEP OUT
OF REACH OF CHILDREN.

Principal Display Panel – Puppies and Small Dogs Carton Label

Elanco

Quad Dewormer

(praziquantel/pyrantel pamoate/febantel)

Chewable Tablets for Dogs

Broad Spectrum Chewable Anthelmintic
for Puppies and Small Dogs (2-25 lbs)

Whipworm
Tapeworm
Hookworm
Roundworm

4
Chewable Tablets
for Dogs

EACH TABLET CONTAINS:

22.7 mg praziquantel,
22.7 mg pyrantel base
as pyrantel pamoate,
and 113.4 mg febantel

Manufactured for: Elanco US Inc. Indianapolis, IN 46221 U.S.A.
Approved by FDA under NADA # 141-007
Patent information at http://www.elancopatents.com

WARNING: KEEP OUT
OF REACH OF CHILDREN.